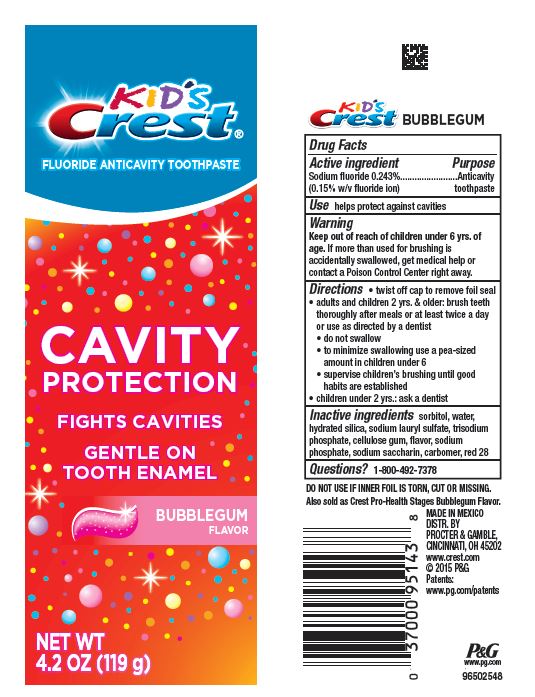 DRUG LABEL: Crest Kids
NDC: 58933-023 | Form: PASTE, DENTIFRICE
Manufacturer: Procter & Gamble Manufactura, S. de R.L. de C.V.
Category: otc | Type: HUMAN OTC DRUG LABEL
Date: 20250612

ACTIVE INGREDIENTS: SODIUM FLUORIDE 1.5 mg/1 g
INACTIVE INGREDIENTS: SORBITOL; WATER; HYDRATED SILICA; SODIUM LAURYL SULFATE; CARBOXYMETHYLCELLULOSE SODIUM; SODIUM PHOSPHATE; SACCHARIN SODIUM; D&C RED NO. 28

Crest Kids SparkleFun Bubblegum

Active ingredient

Sodium fluoride 0.243%
(0.15% w/v fluoride ion)

Purpose

Anticavity toothpaste

Use

helps protect against cavities

WARNINGS

Warning

Keep out of reach of children under 6 yrs. of age. If more than used for brushing is accidentally swallowed, get medical help or contact a Poison Control Center right away.

Directions

- twist off cap to remove foil seal
- adults and children 2 yrs. & older: brush teeth thoroughly after meals or at least twice a day or use as directed by a dentist
- do not swallow
- to minimize swallowing use a pea-sized amount in children under 6
- supervise children’s brushing until good habits are established
- children under 2 yrs.: ask a dentist

Inactive ingredients

sorbitol, water, hydrated silica, sodium lauryl sulfate, trisodium phosphate, cellulose gum, flavor, sodium phosphate, sodium saccharin, carbomer, red 28

Questions?

1-800-492-7378

MADE in Mexico
Dist. by Procter & Gamble,
Cincinnati, OH 45202

PRINCIPAL DISPLAY PANEL - 119 g Tube Label

KId's

Crest

Fluoride Anticavity Toothpaste

Cavity Protection

Fights Cavities

Gentle on Tooth Enamel

Bubblegum Flavor

Net Wt 4.2OZ (119 g)